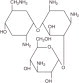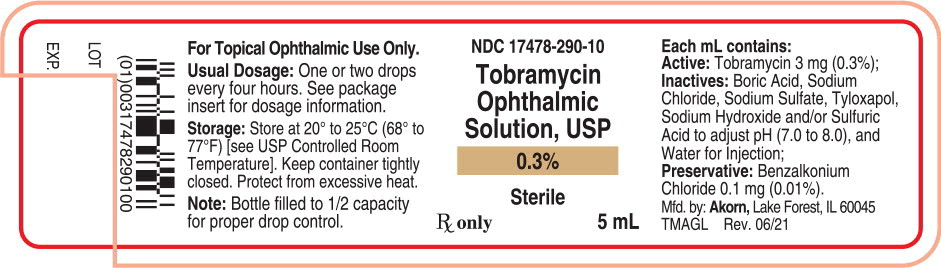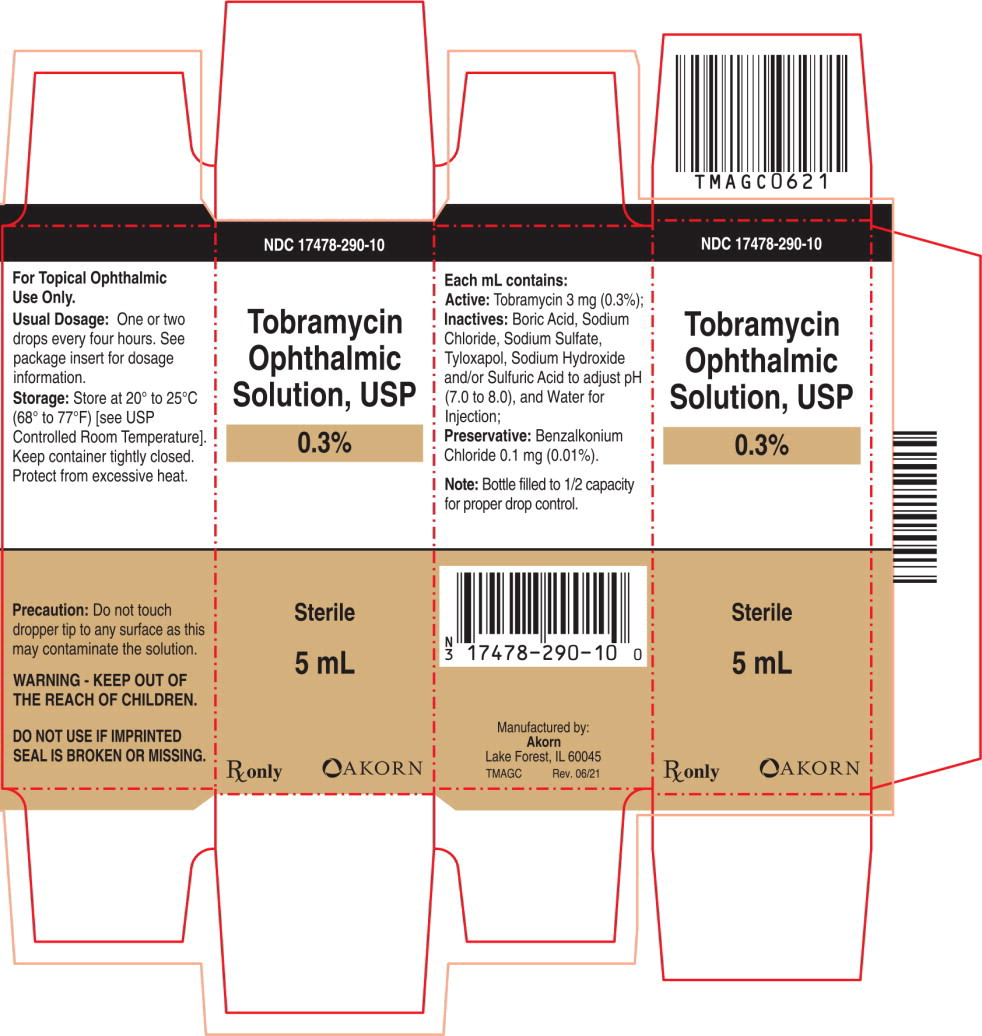 DRUG LABEL: Tobramycin
NDC: 17478-290 | Form: SOLUTION/ DROPS
Manufacturer: Akorn
Category: prescription | Type: HUMAN PRESCRIPTION DRUG LABEL
Date: 20220914

ACTIVE INGREDIENTS: Tobramycin 3 mg/1 mL
INACTIVE INGREDIENTS: Boric Acid; Sodium Chloride; sodium Sulfate; Tyloxapol; Sodium Hydroxide; Sulfuric Acid; WATER; Benzalkonium Chloride

Tobramycin Ophthalmic Solution, USP 0.3%

DESCRIPTION

Tobramycin Ophthalmic Solution USP, 0.3% is a sterile topical ophthalmic antibiotic formulation prepared specifically for topical therapy of external ophthalmic infections.

Each mL contains:

Active: tobramycin 0.3% (3 mg). Inactives: boric acid, sodium chloride, sodium sulfate, tyloxapol, sodium hydroxide and/or sulfuric acid to adjust pH (7.0 to 8.0), and water for injection. Preservative: benzalkonium chloride 0.01% (0.1 mg).

Tobramycin is a water-soluble aminoglycoside antibiotic active against a wide variety of gram-negative and gram-positive ophthalmic pathogens.

The chemical structure of tobramycin is:

Molecular Weight = 467.52

Molecular Formula: C18H37N5O9

Chemical Name:

O-{3-amino-3-deoxy-α-D-gluco-pyranosyl-(1→4)}-O-{2,6-diamino-2,3,6-trideoxy-α-D-ribohexo-pyranosyl-(1→6)}-2- deoxystreptamine.

CLINICAL PHARMACOLOGY

In Vitro Data: In Vitro studies have demonstrated tobramycin is active against susceptible strains of the following microorganisms: Staphylococci, including S. aureus and S. epidermidis (coagulase-positive and coagulase-negative), including penicillin-resistant strains.

Streptococci, including some of the Group A beta-hemolytic species, some nonhemolytic species, and some Streptococcus pneumoniae.

Pseudomonas aeruginosa, Escherichia coli, Klebsiella pneumoniae, Enterobacter aerogenes, Proteus mirabilis, Morganella morganii, most Proteus vulgaris strains, Haemophilus influenzae and H. aegyptius, Moraxella lacunata, Acinetobacter calcoaceticus and some Neisseria species. Bacterial susceptibility studies demonstrate that in some cases, microorganisms resistant to gentamicin retain susceptibility to tobramycin.

INDICATIONS AND USAGE

Tobramycin ophthalmic solution 0.3% is a topical antibiotic indicated in the treatment of external infections of the eye and its adnexa caused by susceptible bacteria. Appropriate monitoring of bacterial response to topical antibiotic therapy should accompany the use of tobramycin ophthalmic solution. Clinical studies have shown tobramycin to be safe and effective for use in children.

CONTRAINDICATIONS

Tobramycin ophthalmic solution 0.3% is contraindicated in patients with known hypersensitivity to any of its components.

WARNINGS

FOR TOPICAL OPHTHALMIC USE. NOT FOR INJECTION INTO THE EYE.

Sensitivity to topically applied aminoglycosides may occur in some patients. Severity of hypersensitivity reactions may vary from local effects to generalized reactions such as erythema, itching, urticaria, skin rash, anaphylaxis, anaphylactoid reactions, or bullous reactions. If a sensitivity reaction to tobramycin ophthalmic solution 0.3% occurs, discontinue use.

PRECAUTIONS

GENERAL PRECAUTIONS

General: As with other antibiotic preparations, prolonged use may result in overgrowth of nonsusceptible organisms, including fungi. If superinfection occurs, appropriate therapy should be initiated.

Cross-sensitivity to other aminoglycoside antibiotics may occur; if hypersensitivity develops with this product, discontinue use and institute appropriate therapy. Patients should be advised not to wear contact lenses if they have signs and symptoms of bacterial ocular infection.

PATIENT COUNSELING INFORMATION

Information for Patients: Do not touch dropper tip to any surface, as this may contaminate the solution.

PREGNANCY

Pregnancy: Reproduction studies in 3 types of animals at doses up to 33 times the normal human systemic dose have revealed no evidence of impaired fertility or harm to the fetus due to tobramycin. There are, however, no adequate and well controlled studies in pregnant women. Because animal studies are not always predictive of human response, this drug should be used during pregnancy only if clearly needed.

NURSING MOTHERS

Nursing Mothers: Because of the potential for adverse reactions in nursing infants from tobramycin, a decision should be made whether to discontinue nursing the infant or discontinue the drug, taking into account the importance of the drug to the mother.

PEDIATRIC USE

Pediatric Use: Safety and effectiveness in pediatric patients below the age of 2 months has not been established.

GERIATRIC USE

Geriatric Use: No overall clinical differences in safety or effectiveness have been observed between the elderly and younger patients.

ADVERSE REACTIONS:

The most frequent adverse reactions to tobramycin ophthalmic solution 0.3% are hypersensitivity and localized ocular toxicity, including lid itching and swelling, and conjunctival erythema. These reactions occur in less than three of 100 patients treated with tobramycin.

POSTMARKETING EXPERIENCE

Postmarketing Experience: Additional adverse reactions identified from postmarketing use include anaphylactic reaction, Stevens-Johnson syndrome, and erythema multiforme.

The following additional adverse reactions have been reported with systemic aminoglycosides: Neurotoxicity, ototoxicity and nephrotoxicity have occurred in patients receiving systemic aminoglycoside therapy. Aminoglycosides may aggravate muscle weakness in patients with known or suspected neuromuscular disorders, such as myasthenia gravis or Parkinson's disease, because of their potential effect on neuromuscular function.

DOSAGE AND ADMINISTRATION

In mild to moderate disease, instill 1 or 2 drops into the affected eye(s) every 4 hours. In severe infections, instill 2 drops into the eye(s) hourly until improvement, following which treatment should be reduced prior to discontinuation.

HOW SUPPLIED

Tobramycin Ophthalmic Solution USP, 0.3% is supplied as a sterile solution in white low-density polyethylene (LDPE) plastic dropper bottles in two sizes:

NDC 17478-290-20 . . . . . . . . . . . . 2 mL

NDC 17478-290-10 . . . . . . . . . . . . 5 mL

STORAGE

Store at 20° to 25°C (68° to 77°F) [see USP Controlled Room Temperature]. Keep container tightly closed. Protect from excessive heat.

AKORN
Manufactured by: Akorn
Lake Forest, IL 60045

GTM00N Rev. 06/21

Principal Display Panel Text for Container Label:

NDC 17478-290-10

Tobramycin

Ophthalmic

Solution, USP

0.3%

Sterile

Rx only 5mL

Principal Display Panel Text for Carton Label:

NDC 17478-290-10

Tobramycin

Ophthalmic

Solution, USP

0.3%

Sterile

5 mL

Rx only Akorn